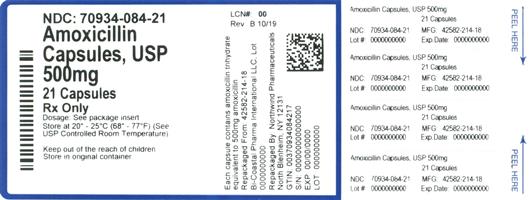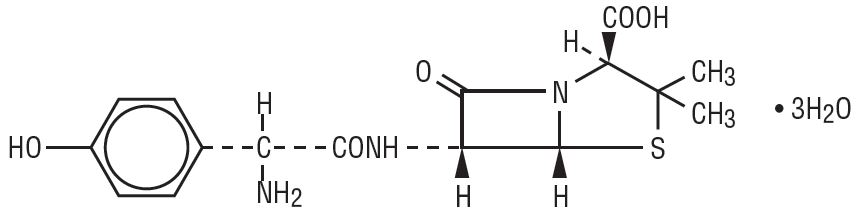 DRUG LABEL: Amoxicillin
NDC: 70934-084 | Form: CAPSULE
Manufacturer: Denton Pharma, Inc. DBA Northwind Pharmaceuticals
Category: prescription | Type: HUMAN PRESCRIPTION DRUG LABEL
Date: 20210101

ACTIVE INGREDIENTS: AMOXICILLIN 500 mg/1 1
INACTIVE INGREDIENTS: MAGNESIUM STEARATE; SODIUM LAURYL SULFATE; D&C YELLOW NO. 10; FD&C YELLOW NO. 6; TITANIUM DIOXIDE; GELATIN

Amoxicillin Capsules, USP 250 mg and 500 mg

Rx only

To reduce the development of drug-resistant bacteria and maintain the effectiveness of amoxicillin and other antibacterial drugs, amoxicillin is to be used only to treat or prevent infections that are proven or strongly suspected to be caused by bacteria.

DESCRIPTION

Formulations of amoxicillin capsules, USP contain amoxicillin, a semi-synthetic antibiotic, an analog of ampicillin, with a broad spectrum of bactericidal activity against many gram-positive and gram-negative microorganisms. Chemically, it is (2 S, 5 R, 6 R)-6-[(R)-(-)-2-amino-2-(p-hydroxyphenyl) acetamido] -3,3-dimethyl-7-oxo-4-thia-1-azabicyclo [3.2.0] heptane-2-carboxylic acid trihydrate. It may be represented structurally as:

The amoxicillin molecular formula is C16H19N3O5S∙3H2O, and the molecular weight is 419.45.

Capsules of Amoxicillin are intended for oral administration.

Each capsule contains amoxicillin trihydrate equivalent to 250 mg or 500 mg amoxicillin.

Caramel opaque cap and buff opaque body of the 250 mg capsule are imprinted with AA and 820 respectively. Each 250 mg capsule contains the following inactive ingredients: magnesium stearate, sodium lauryl sulfate, D&C Yellow No. 10, FD&C Yellow No. 6, FD&C Blue No. 1, FD&C Red No. 3, titanium dioxide and gelatin.

Buff opaque cap and buff opaque body of the 500 mg capsule are imprinted with AA and 825 respectively. Each 500 mg capsule contains the following inactive ingredients: magnesium stearate, sodium lauryl sulfate, D&C Yellow No. 10, FD&C Yellow No. 6, titanium dioxide and gelatin.

CLINICAL PHARMACOLOGY

Amoxicillin is stable in the presence of gastric acid and is rapidly absorbed after oral administration. The effect of food on the absorption of amoxicillin from the tablets and suspension of amoxicillin has been partially investigated. The 400 mg and 875 mg formulations have been studied only when administered at the start of a light meal. However, food effect studies have not been performed with the 200 mg and 500 mg formulations. Amoxicillin diffuses readily into most body tissues and fluids, with the exception of brain and spinal fluid, except when meninges are inflamed. The half-life of amoxicillin is 61.3 minutes. Most of the amoxicillin is excreted unchanged in the urine; its excretion can be delayed by concurrent administration of probenecid. In blood serum, amoxicillin is approximately 20% protein-bound.

Orally administered doses of 250 mg and 500 mg amoxicillin capsules result in average peak blood levels 1 to 2 hours after administration in the range of 3.5 mcg/mL to 5.0 mcg/mL and 5.5 mcg/mL to 7.5 mcg/mL, respectively.

Mean amoxicillin pharmacokinetic parameters from an open, two-part, single-dose crossover bioequivalence study in 27 adults comparing 875 mg of amoxicillin with 875 mg of amoxicillin and clavulanate potassium showed that the 875 mg tablet of amoxicillin produces an AUCo-∞ of 35.4 ± 8.1 mcg•hr/mL and a Cmax of 13.8 ± 4.1 mcg/mL. Dosing was at the start of a light meal following an overnight fast.

Orally administered doses of amoxicillin suspension, 125 mg/5 mL and 250 mg/5 mL, result in average peak blood levels 1 to 2 hours after administration in the range of 1.5 mcg/mL to 3.0 mcg/mL and 3.5 mcg/mL to 5.0 mcg/mL, respectively.

Oral administration of single doses of 400 mg chewable tablets and 400 mg/5 mL suspension of amoxicillin to 24 adult volunteers yielded comparable pharmacokinetic data:

Dose* | AUC0 - ∞ (mcg∙hr/mL) | Cmax (mcg/mL)†
Amoxicillin | Amoxicillin (±S.D.) | Amoxicillin (±S.D.)
400 mg (5 mL of suspension) | 17.1 (3.1) | 5.92 (1.62)
400 mg (1 chewable tablet) | 17.9 (2.4) | 5.18 (1.64)
* Administered at the start of a light meal.
† Mean values of 24 normal volunteers. Peak concentrations occurred approximately 1 hour after the dose.

Detectable serum levels are observed up to 8 hours after an orally administered dose of amoxicillin. Following a 1 gram dose and utilizing a special skin window technique to determine levels of the antibiotic, it was noted that therapeutic levels were found in the interstitial fluid. Approximately 60% of an orally administered dose of amoxicillin is excreted in the urine within 6 to 8 hours.

Microbiology

Amoxicillin is similar to ampicillin in its bactericidal action against susceptible organisms during the stage of active multiplication. It acts through the inhibition of biosynthesis of cell wall mucopeptide. Amoxicillin has been shown to be active against most strains of the following microorganisms, both in vitro and in clinical infections as described in the INDICATIONS AND USAGE section.

Aerobic Gram-Positive Microorganisms

Enterococcus faecalis

Staphylococcus spp.* (β-lactamase-negative strains only)

Streptococcus pneumoniae

Streptococcus spp. (α- and β-hemolytic strains only)

*Staphylococci which are susceptible to amoxicillin but resistant to methicillin/oxacillin
should be considered as resistant to amoxicillin.

Aerobic Gram-Negative Microorganisms

Escherichia coli (β-lactamase-negative strains only)

Haemophilus influenzae (β-lactamase-negative strains only)

Neisseria gonorrhoeae (β-lactamase-negative strains only)

Proteus mirabilis (β-lactamase-negative strains only)

Helicobacter

Helicobacter pylori

Susceptibility Tests

Dilution Techniques

Quantitative methods are used to determine antimicrobial minimum inhibitory concentrations (MICs). These MICs provide estimates of the susceptibility of bacteria to antimicrobial compounds. The MICs should be determined using a standardized procedure. Standardized procedures are based on a dilution method^1 (broth or agar) or equivalent with standardized inoculum concentrations and standardized concentrations of ampicillin powder. Ampicillin is sometimes used to predict susceptibility of S. pneumoniae to amoxicillin; however, some intermediate strains have been shown to be susceptible to amoxicillin. Therefore, S. pneumoniae susceptibility should be tested using amoxicillin powder. The MIC values should be interpreted according to the following criteria:

For Gram-Positive Aerobes

Enterococcus

MIC (mcg/mL) | Interpretation
≤ 8 | Susceptible (S)
16 | Resistant (R)
Staphylococcusa
MIC (mcg/mL) | Interpretation
≤ 0.25 | Susceptible (S)
≤ 0.5 | Resistant (R)

S. pneumoniaeb from non-meningitis sources.

(Amoxicillin powder should be used to determine susceptibility.)

MIC (mcg/mL) | Interpretation
≤ 2 | Susceptible (S)
4 | Intermediate (I)
≥ 8 | Resistant (R)

NOTE: These interpretive criteria are based on the recommended doses for respiratory tract infections.

For Gram-Negative Aerobes

Enterobacteriaceae

MIC (mcg/mL) | Interpretation
≤ 8 | Susceptible (S)
16 | Intermediate (I)
≥ 32 | Resistant (R)

H. influenzaec

MIC (mcg/mL) | Interpretation
≤ 1 | Susceptible (S)
2 | Intermediate (I)
≥ 4 | Resistant (R)

1. Staphylococci which are susceptible to amoxicillin but resistant to methicillin/oxacillin should be considered as resistant to amoxicillin.
2. These interpretive standards are applicable only to broth microdilution susceptibility tests using cation-adjusted Mueller-Hinton broth with 2-5% lysed horse blood.
3. These interpretive standards are applicable only to broth microdilution test with H. influenzae using Haemophilus Test Medium (HTM).^1

A report of “Susceptible” indicates that the pathogen is likely to be inhibited if the antimicrobial compound in the blood reaches the concentrations usually achievable. A report of “Intermediate” indicates that the result should be considered equivocal, and, if the microorganism is not fully susceptible to alternative, clinically feasible drugs, the test should be repeated. This category implies possible clinical applicability in body sites where the drug is physiologically concentrated or in situations where high dosage of drug can be used. This category also provides a buffer zone, which prevents small uncontrolled technical factors from causing major discrepancies in interpretation. A report of “Resistant” indicates that the pathogen is not likely to be inhibited if the antimicrobial compound in the blood reaches the concentrations usually achievable; other therapy should be selected.

Standardized susceptibility test procedures require the use of laboratory control microorganisms to control the technical aspects of the laboratory procedures. Standard ampicillin powder should provide the following MIC values:

Microorganism | MIC Range (mcg/mL)
E. coli ATCC 25922 | 2 to 8
E. faecalis ATCC 29212 | 0.5 to 2
H. influenzae ATCC 49247d | 2 to 8
S. aureus ATCC 29213 | 0.25 to 1

Using amoxicillin to determine susceptibility:

Microorganism MIC Range (mcg/mL)

S. pneumoniae ATCC 49619e 0.03 to 0.12

d.This quality control range is applicable to only H. influenzae ATCC 49247 tested by a broth microdilution procedure using HTM.^1e.This quality control range is applicable to only S. pneumoniaeATCC 49619 tested by the broth microdilution procedure using cation-adjusted Mueller- Hinton broth with 2-5% lysed horse blood.

Diffusion Techniques

Quantitative methods that require measurement of zone diameters also provide reproducible estimates of the susceptibility of bacteria to antimicrobial compounds. One such standardized procedure^2 requires the use of standardized inoculum concentrations. This procedure uses paper disks impregnated with 10 mcg ampicillin to test the susceptibility of microorganisms, except S. pneumoniae, to amoxicillin. Interpretation involves correlation of the diameter obtained in the disk test with the MIC for ampicillin.

Reports from the laboratory providing results of the standard single-disk susceptibility test with a 10 mcg ampicillin disk should be interpreted according to the following criteria:

For Gram-Positive Aerobes

Enterococcus

Zone Diameter (mm) | Interpretation
≥ 17 | Susceptible (S)
≥ 16 | Resistant (R)

Staphylococcusf

Zone Diameter (mm) | Interpretation
≥ 29 | Susceptible (S)
≥ 28 | Resistant (R)

β-hemolytic streptococci

Zone Diameter (mm) | Interpretation
≥ 26 | Susceptible (S)
19 to 25 | Intermediate (I)
≤ 18 | Resistant (R)

NOTE: For streptococci (other than β-hemolytic streptococci and S. pneumoniae), an ampicillin MIC should be determined.

S. pneumoniae

S. pneumoniae should be tested using a 1 mcg oxacillin disk. Isolates with oxacillin zone sizes of ≥ 20 mm are susceptible to amoxicillin. An amoxicillin MIC should be determined on isolates of

S. pneumoniae with oxacillin zone sizes of ≤ 19 mm.

For Gram-Negative Aerobes

Enterobacteriaceae

Zone Diameter (mm) | Interpretation
≥ 17 | Susceptible (S)
14 to 16 | Intermediate (I)
≤ 13 | Resistant (R)

H. influenzaeg

Zone Diameter (mm) | Interpretation
≥ 22 | Susceptible (S)
19 to 21 | Intermediate (I)
≤ 18 | Resistant (R)

f.Staphylococci which are susceptible to amoxicillin but resistant to methicillin/oxacillin should be considered as resistant to amoxicillin.g.These interpretive standards are applicable only to disk diffusion susceptibility tests with H. influenzae using Haemophilus Test Medium (HTM).^2

Interpretation should be as stated above for results using dilution techniques.

As with standard dilution techniques, disk diffusion susceptibility test procedures require the use of laboratory control microorganisms. The 10 mcg ampicillin disk should provide the following zone diameters in these laboratory test quality control strains:

Microorganism | Zone diameter (mm)
E. coli ATCC 25922 | 16 to 22
H. influenzae ATCC 49247h | 13 to 21
S. aureus ATCC 25923 | 27 to 35

Using 1 mcg oxacillin disk:

Microorganism | Zone diameter (mm)
S. pneumoniae ATCC 49619i | 8 to 12

h.This quality control range is applicable to only H. influenzae ATCC 49247 tested by a disk diffusion procedure using HTM.^2i.This quality control range is applicable to only S. pneumoniae ATCC 49619 tested by a disk diffusion procedure using Mueller-Hinton agar supplemented with 5% sheep blood and incubated in 5% CO2.

Susceptibility Testing for Helicobacter pylori

In vitro susceptibility testing methods and diagnostic products currently available for determining minimum inhibitory concentrations (MICs) and zone sizes have not been standardized, validated, or approved for testing H. pylori microorganisms.

Culture and susceptibility testing should be obtained in patients who fail triple therapy. If clarithromycin resistance is found, a non-clarithromycin-containing regimen should be used.

INDICATIONS AND USAGE

Amoxicillin is indicated in the treatment of infections due to susceptible (ONLY β-lactamase-negative) strains of the designated microorganisms in the conditions listed below:

Infections of the ear, nose, and throat - due to Streptococcus spp. (α- and β- hemolytic strains only), S. pneumoniae, Staphylococcus spp., or H. influenzae.

Infections of the genitourinary tract - due to E. coli, P. mirabilis, or E. faecalis.

Infections of the skin and skin structure - due to Streptococcus spp. (α- and β-hemolytic strains only), Staphylococcus spp., or E. coli.

Infections of the lower respiratory tract - due to Streptococcus spp. (α- and β-hemolytic strains only), S. pneumoniae, Staphylococcus spp., or H. influenzae.

Gonorrhea, acute uncomplicated (ano-genital and urethral infections) - due to N. gonorrhoeae (males and females).

H. pylori eradication to reduce the risk of duodenal ulcer recurrence.

Triple Therapy

Amoxicillin/Clarithromycin/Lansoprazole

Amoxicillin, in combination with clarithromycin plus lansoprazole as triple therapy, is indicated for the treatment of patients with H. pylori infection and duodenal ulcer disease (active or 1-year history of a duodenal ulcer) to eradicate H. pylori. Eradication of H. pylori has been shown to reduce the risk of duodenal ulcer recurrence. (See CLINICAL STUDIES and DOSAGE AND ADMINISTRATION sections.)

Dual Therapy

Amoxicillin/Lansoprazole

Amoxicillin, in combination with lansoprazole delayed-release capsules as dual therapy, is indicated for the treatment of patients with H. pylori infection and duodenal ulcer disease (active or 1-year history of a duodenal ulcer) who are either allergic or intolerant to clarithromycin or in whom resistance to clarithromycin is known or suspected. (See the clarithromycin package insert, MICROBIOLOGY section.) Eradication of H. pylori has been shown to reduce the risk of duodenal ulcer recurrence. (See CLINICAL STUDIESand DOSAGE AND ADMINISTRATION sections.)

To reduce the development of drug-resistant bacteria and maintain the effectiveness of amoxicillin and other antibacterial drugs, amoxicillin should be used only to treat or prevent infections that are proven or strongly suspected to be caused by susceptible bacteria. When culture and susceptibility information are available, they should be considered in selecting or modifying antibacterial therapy. In the absence of such data, local epidemiology and susceptibility patterns may contribute to the empiric selection of therapy.

Indicated surgical procedures should be performed.

CONTRAINDICATIONS

A history of allergic reaction to any of the penicillins is a contraindication.

WARNINGS

SERIOUS AND OCCASIONALLY FATAL HYPERSENSITIVITY (ANAPHYLACTIC) REACTIONS HAVE BEEN REPORTED IN PATIENTS ON PENICILLIN THERAPY. ALTHOUGH ANAPHYLAXIS IS MORE FREQUENT FOLLOWING PARENTERAL THERAPY, IT HAS OCCURRED IN PATIENTS ON ORAL PENICILLINS. THESE REACTIONS ARE MORE LIKELY TO OCCUR IN INDIVIDUALS WITH A HISTORY OF PENICILLIN HYPERSENSITIVITY AND/OR A HISTORY OF SENSITIVITY TO MULTIPLE ALLERGENS. THERE HAVE BEEN REPORTS OF INDIVIDUALS WITH A HISTORY OF PENICILLIN HYPERSENSITIVITY WHO HAVE EXPERIENCED SEVERE REACTIONS WHEN TREATED WITH CEPHALOSPORINS. BEFORE INITIATING THERAPY WITH AMOXICILLIN, CAREFUL INQUIRY SHOULD BE MADE CONCERNING PREVIOUS HYPERSENSITIVITY REACTIONS TO PENICILLINS, CEPHALOSPORINS, OR OTHER ALLERGENS. IF AN ALLERGIC REACTION OCCURS, AMOXICILLIN SHOULD BE DISCONTINUED AND APPROPRIATE THERAPY INSTITUTED. SERIOUS ANAPHYLACTIC REACTIONS REQUIRE IMMEDIATE EMERGENCY TREATMENT WITH EPINEPHRINE. OXYGEN, INTRAVENOUS STEROIDS, AND AIRWAY MANAGEMENT, INCLUDING INTUBATION, SHOULD ALSO BE ADMINISTERED AS INDICATED.

Clostridium difficile associated diarrhea (CDAD) has been reported with use of nearly all antibacterial agents, including amoxicillin, and may range in severity from mild diarrhea to fatal colitis. Treatment with antibacterial agents alters the normal flora of the colon leading to overgrowth of C. difficile.

C. difficile produces toxins A and B which contribute to the development of CDAD. Hypertoxin producing strains of C. difficile cause increased morbidity and mortality, as these infections can be refractory to antimicrobial therapy and may require colectomy. CDAD must be considered in all patients who present with diarrhea following antibiotic use. Careful medical history is necessary since CDAD has been reported to occur over two months after the administration of antibacterial agents.

If CDAD is suspected or confirmed, ongoing antibiotic use not directed against C. difficile may need to be discontinued. Appropriate fluid and electrolyte management, protein supplementation, antibiotic treatment of C. difficile, and surgical evaluation should be instituted as clinically indicated.

PRECAUTIONS

General

The possibility of superinfections with mycotic or bacterial pathogens should be kept in mind during therapy. If superinfections occur, amoxicillin should be discontinued and appropriate therapy instituted.

A high percentage of patients with mononucleosis who receive ampicillin develop an erythematous skin rash. Thus, ampicillin-class antibiotics should not be administered to patients with mononucleosis.

Prescribing amoxicillin in the absence of a proven or strongly suspected bacterial infection or a prophylactic indication is unlikely to provide benefit to the patient and increases the risk of the development of drug-resistant bacteria.

Laboratory Tests

As with any potent drug, periodic assessment of renal, hepatic, and hematopoietic function should be made during prolonged therapy.

All patients with gonorrhea should have a serologic test for syphilis at the time of diagnosis. Patients treated with amoxicillin should have a follow-up serologic test for syphilis after 3 months.

Drug Interactions

Probenecid decreases the renal tubular secretion of amoxicillin. Concurrent use of amoxicillin and probenecid may result in increased and prolonged blood levels of amoxicillin.

Chloramphenicol, macrolides, sulfonamides, and tetracyclines may interfere with the bactericidal effects of penicillin. This has been demonstrated in vitro; however, the clinical significance of this interaction is not well documented.

In common with other antibiotics, amoxicillin may affect the gut flora, leading to lower estrogen reabsorption and reduced efficacy of combined oral estrogen/progesterone contraceptives.

Drug/Laboratory Test Interactions

High urine concentrations of ampicillin may result in false-positive reactions when testing for the presence of glucose in urine using CLINITEST®, Benedict’s Solution, or Fehling’s Solution. Since this effect may also occur with amoxicillin, it is recommended that glucose tests based on enzymatic glucose oxidase reactions (such as CLINISTIX®) be used.

Following administration of ampicillin to pregnant women, a transient decrease in plasma concentration of total conjugated estriol, estriol-glucuronide, conjugated estrone, and estradiol has been noted. This effect may also occur with amoxicillin.

Carcinogenesis, Mutagenesis, Impairment of Fertility

Long-term studies in animals have not been performed to evaluate carcinogenic potential. Studies to detect mutagenic potential of amoxicillin alone have not been conducted; however, the following information is available from tests on a 4:1 mixture of amoxicillin and potassium clavulanate. Amoxicillin and potassium clavulanate was non-mutagenic in the Ames bacterial mutation assay, and the yeast gene conversion assay. Amoxicillin and potassium clavulanate was weakly positive in the mouse lymphoma assay, but the trend toward increased mutation frequencies in this assay occurred at doses that were also associated with decreased cell survival. Amoxicillin and potassium clavulanate was negative in the mouse micronucleus test, and in the dominant lethal assay in mice. Potassium clavulanate alone was tested in the Ames bacterial mutation assay and in the mouse micronucleus test, and was negative in each of these assays. In a multi-generation reproduction study in rats, no impairment of fertility or other adverse reproductive effects were seen at doses up to 500 mg/kg (approximately 3 times the human dose in mg/m^2).

Pregnancy

Teratogenic Effects

Pregnancy Category B.

Reproduction studies have been performed in mice and rats at doses up to 10 times the human dose and have revealed no evidence of impaired fertility or harm to the fetus due to amoxicillin. There are, however, no adequate and well-controlled studies in pregnant women. Because animal reproduction studies are not always predictive of human response, this drug should be used during pregnancy only if clearly needed.

Labor and Delivery

Oral ampicillin-class antibiotics are poorly absorbed during labor. Studies in guinea pigs showed that intravenous administration of ampicillin slightly decreased the uterine tone and frequency of contractions but moderately increased the height and duration of contractions. However, it is not known whether use of amoxicillin in humans during labor or delivery has immediate or delayed adverse effects on the fetus, prolongs the duration of labor, or increases the likelihood that forceps delivery or other obstetrical intervention or resuscitation of the newborn will be necessary.

Nursing Mothers

Penicillins have been shown to be excreted in human milk. Amoxicillin use by nursing mothers may lead to sensitization of infants. Caution should be exercised when amoxicillin is administered to a nursing woman.

Pediatric Use

Because of incompletely developed renal function in neonates and young infants, the elimination of amoxicillin may be delayed. Dosing of amoxicillin should be modified in pediatric patients 12 weeks or younger (≤ 3 months). (See DOSAGE AND ADMINISTRATION: Neonates and Infants section.)

Geriatric Use

An analysis of clinical studies of amoxicillin was conducted to determine whether subjects aged 65 and over respond differently from younger subjects. Of the 1,811 subjects treated with amoxicillin capsules, 85% were < 60 years old, 15% were ≥ 61 years old and 7% were ≥ 71 years old. This analysis and other reported clinical experience have not identified differences in responses between the elderly and younger patients, but a greater sensitivity of some older individuals cannot be ruled out.

This drug is known to be substantially excreted by the kidney, and the risk of toxic reactions to this drug may be greater in patients with impaired renal function. Because elderly patients are more likely to have decreased renal function, care should be taken in dose selection, and it may be useful to monitor renal function.

Information for Patients

Amoxicillin may be taken every 8 hours or every 12 hours, depending on the strength of the product prescribed.

Patients should be counseled that antibacterial drugs, including amoxicillin, should only be used to treat bacterial infections. They do not treat viral infections (e.g., the common cold). When amoxicillin is prescribed to treat a bacterial infection, patients should be told that although it is common to feel better early in the course of therapy, the medication should be taken exactly as directed. Skipping doses or not completing the full course of therapy may: (1) decrease the effectiveness of the immediate treatment, and (2) increase the likelihood that bacteria will develop resistance and will not be treatable by amoxicillin or other antibacterial drugs in the future.

Diarrhea is a common problem caused by antibiotics which usually ends when the antibiotic is discontinued. Sometimes after starting treatment with antibiotics, patients can develop watery and bloody stools (with or without stomach cramps and fever) even as late as 2 or more months after having taken the last dose of the antibiotic. If this occurs, patients should contact their physician as soon as possible.

ADVERSE REACTIONS

As with other penicillins, it may be expected that untoward reactions will be essentially limited to sensitivity phenomena. They are more likely to occur in individuals who have previously demonstrated hypersensitivity to penicillins and in those with a history of allergy, asthma, hay fever, or urticaria. The following adverse reactions have been reported as associated with the use of penicillins:

Infections and Infestations: Mucocutaneous candidiasis.

Gastrointestinal: Nausea, vomiting, diarrhea, black hairy tongue, and hemorrhagic/ pseudomembranous colitis.

Onset of pseudomembranous colitis symptoms may occur during or after antibiotic treatment. (See WARNINGS section.)

Hypersensitivity Reactions: Anaphylaxis (See WARNINGS section)

Serum sickness-like reactions, erythematous maculopapular rashes, erythema multiforme, Stevens-Johnson syndrome, exfoliative dermatitis, toxic epidermal necrolysis, acute generalized exanthematous pustulosis, hypersensitivity vasculitis and urticaria have been reported.

NOTE: These hypersensitivity reactions may be controlled with antihistamines and, if necessary, systemic corticosteroids. Whenever such reactions occur, amoxicillin should be discontinued unless, in the opinion of the physician, the condition being treated is life-threatening and amenable only to amoxicillin therapy.

Liver: A moderate rise in AST (SGOT) and/or ALT (SGPT) has been noted, but the significance of this finding is unknown. Hepatic dysfunction including cholestatic jaundice, hepatic cholestasis and acute cytolytic hepatitis have been reported.

Renal: Crystalluria has also been reported (see OVERDOSAGE section).

Hemic and Lymphatic Systems: Anemia, including hemolytic anemia, thrombocytopenia, thrombocytopenic purpura, eosinophilia, leukopenia, and agranulocytosis have been reported during therapy with penicillins. These reactions are usually reversible on discontinuation of therapy and are believed to be hypersensitivity phenomena.

Central Nervous System: Reversible hyperactivity, agitation, anxiety, insomnia, confusion, convulsions, behavioral changes, and/or dizziness have been reported rarely.

Miscellaneous: Tooth discoloration (brown, yellow, or gray staining) has been rarely reported. Most reports occurred in pediatric patients. Discoloration was reduced or eliminated with brushing or dental cleaning in most cases.

Combination Therapy with Clarithromycin and Lansoprazole

In clinical trials using combination therapy with amoxicillin plus clarithromycin and lansoprazole, and amoxicillin plus lansoprazole, no adverse reactions peculiar to these drug combinations were observed. Adverse reactions that have occurred have been limited to those that had been previously reported with amoxicillin, clarithromycin, or lansoprazole.

Triple Therapy

Amoxicillin/Clarithromycin/Lansoprazole

The most frequently reported adverse events for patients who received triple therapy were diarrhea (7%), headache (6%), and taste perversion (5%). No treatment-emergent adverse events were observed at significantly higher rates with triple therapy than with any dual therapy regimen.

Dual Therapy

Amoxicillin/Lansoprazole

The most frequently reported adverse events for patients who received amoxicillin three times daily plus lansoprazole three times daily dual therapy were diarrhea (8%) and headache (7%). No treatment-emergent adverse events were observed at significantly higher rates with amoxicillin three times daily plus lansoprazole three times daily dual therapy than with lansoprazole alone.

For more information on adverse reactions with clarithromycin or lansoprazole, refer to their package inserts, ADVERSE REACTIONS section.

OVERDOSAGE

In case of overdosage, discontinue medication, treat symptomatically, and institute supportive measures as required. If the overdosage is very recent and there is no contraindication, an attempt at emesis or other means of removal of drug from the stomach may be performed. A prospective study of 51 pediatric patients at a poison-control center suggested that overdosages of less than 250 mg/kg of amoxicillin are not associated with significant clinical symptoms and do not require gastric emptying.^3

Interstitial nephritis resulting in oliguric renal failure has been reported in a small number of patients after overdosage with amoxicillin.

Crystalluria, in some cases leading to renal failure, has also been reported after amoxicillin overdosage in adult and pediatric patients. In case of overdosage, adequate fluid intake and diuresis should be maintained to reduce the risk of amoxicillin crystalluria.

Renal impairment appears to be reversible with cessation of drug administration. High blood levels may occur more readily in patients with impaired renal function because of decreased renal clearance of amoxicillin. Amoxicillin may be removed from circulation by hemodialysis.

DOSAGE AND ADMINISTRATION

Amoxicillin capsules may be given without regard to meals.

Neonates and Infants Aged ≤ 12 Weeks (≤ 3 Months)

Due to incompletely developed renal function affecting elimination of amoxicillin in this age group, the recommended upper dose of amoxicillin is 30 mg/kg/day divided q12h.

Adults and Pediatric Patients > 3 Months

Infection | Severity* | Usual Adult Dose | Usual Dose for Children >3 Months†
Ear/Nose/ Throat | Mild/ Moderate | 500 mg every 12 hours or 250 mg every 8 hours | 25 mg/kg/day in divided doses every 12 hours or 20 mg/kg/day in divided doses every 8 hours
Ear/Nose/ Throat | Severe | 875 mg every 12 hours or 500 mg every 8 hours | 45 mg/kg/day in divided doses every 12 hours or 40 mg/kg/day in divided doses every 8 hours
Lower Respiratory Tract | Mild/ Moderate or Severe | 875 mg every 12 hours or 500 mg every 8 hours | 45 mg/kg/day in divided doses every 12 hours or 40 mg/kg/day in divided doses every 8 hours
Skin/Skin Structure | Mild/ Moderate | 500 mg every 12 hours or 250 mg every 8 hours | 25 mg/kg/day in divided doses every 12 hours or 20 mg/kg/day in divided doses every 8 hours
Skin/Skin Structure | Severe | 875 mg every 12 hours or 500 mg every 8 hours | 45 mg/kg/day in divided doses every 12 hours or 40 mg/kg/day in divided doses every 8 hours
Genitourinary Tract | Mild/ Moderate | 500 mg every 12 hours or 250 mg every 8 hours | 25 mg/kg/day in divided doses every 12 hours or 20 mg/kg/day in divided doses every 8 hours
Genitourinary Tract | Severe | 875 mg every 12 hours or 500 mg every 8 hours | 45 mg/kg/day in divided doses every 12 hours or 40 mg/kg/day in divided doses every 8 hours
Gonorrhea Acute, uncomplicated ano-genital and urethral infections in males and females |  | 3 grams as single oral dose | Prepubertal children: 50 mg/kg Amoxicillin, combined with 25 mg/kg probenecid as a single dose. NOTE: SINCE PROBENECID IS CONTRAINDICATED IN CHILDREN UNDER 2 YEARS, DO NOT USE THIS REGIMEN IN THESE CASES.
* Dosing for infections caused by less susceptible organisms should follow the recommendations for severe infections.
† The children’s dosage is intended for individuals whose weight is less than 40 kg. Children weighing 40 kg or more should be dosed according to the adult recommendations.

All patients with gonorrhea should be evaluated for syphilis. (See PRECAUTIONS: Laboratory Tests section.)

Larger doses may be required for stubborn or severe infections.

General

It should be recognized that in the treatment of chronic urinary tract infections, frequent bacteriological and clinical appraisals are necessary. Smaller doses than those recommended above should not be used. Even higher doses may be needed at times. In stubborn infections, therapy may be required for several weeks. It may be necessary to continue clinical and/or bacteriological follow-up for several months after cessation of therapy. Except for gonorrhea, treatment should be continued for a minimum of 48 to 72 hours beyond the time that the patient becomes asymptomatic or evidence of bacterial eradication has been obtained. It is recommended that there be at least 10 days’ treatment for any infection caused by Streptococcus pyogenes to prevent the occurrence of acute rheumatic fever.

H. pylori Eradication to Reduce the Risk of Duodenal Ulcer Recurrence

Triple Therapy

Amoxicillin/Clarithromycin/Lansoprazole

The recommended adult oral dose is 1 gram amoxicillin, 500 mg clarithromycin, and 30 mg lansoprazole, all given twice daily (q12h) for 14 days. (See INDICATIONS AND USAGE section.)

Dual Therapy

Amoxicillin/Lansoprazole

The recommended adult oral dose is 1 gram amoxicillin and 30 mg lansoprazole, each given three times daily (q8h) for 14 days. (See INDICATIONS AND USAGE section.)

Please refer to clarithromycin and lansoprazole full prescribing information for CONTRAINDICATIONS and WARNINGS section, and for information regarding dosing in elderly and renally impaired patients.

Dosing Recommendations for Adults with Impaired Renal Function

Patients with impaired renal function do not generally require a reduction in dose unless the impairment is severe. Severely impaired patients with a glomerular filtration rate of < 30 mL/min should not receive the 875 mg tablet. Patients with a glomerular filtration rate of 10 to 30 mL/min should receive 500 mg or 250 mg every 12 hours, depending on the severity of the infection. Patients with a less than 10 mL/min glomerular filtration rate should receive 500 mg or 250 mg every 24 hours, depending on severity of the infection.

Hemodialysis patients should receive 500 mg or 250 mg every 24 hours, depending on severity of the infection. They should receive an additional dose both during and at the end of dialysis.

There are currently no dosing recommendations for pediatric patients with impaired renal function.

HOW SUPPLIED

Each capsule contains amoxicillin trihydrate equivalent to 500 mg amoxicillin.

500 mg Capsule

Buff opaque cap and buff opaque body of the 500 mg capsule are imprinted with AA and 825 respectively.

NDC 70934-084-21 bottles of 21
NDC 70934-084-30 bottles of 30

Store capsules at 20 o C to 25 o C (68 o F to 77 o F) [See USP Controlled Room Temperature]

CLINICAL STUDIES

H. pylori Eradication to Reduce the Risk of Duodenal Ulcer Recurrence

Randomized, double-blind clinical studies performed in the United States in patients with H. pylori and duodenal ulcer disease (defined as an active ulcer or history of an ulcer within 1 year) evaluated the efficacy of lansoprazole in combination with amoxicillin capsules and clarithromycin tablets as triple 14-day therapy, or in combination with amoxicillin capsules as dual 14-day therapy, for the eradication of H. pylori. Based on the results of these studies, the safety and efficacy of 2 different eradication regimens were established:

Triple Therapy

Amoxicillin 1 gram twice daily/clarithromycin 500 mg twice daily/lansoprazole 30 mg twice daily.

Dual Therapy

Amoxicillin 1 gram three times daily/lansoprazole 30 mg three times daily.

All treatments were for 14 days. H. pylori eradication was defined as 2 negative tests (culture and histology) at 4 to 6 weeks following the end of treatment.

Triple therapy was shown to be more effective than all possible dual therapy combinations. Dual therapy was shown to be more effective than both monotherapies. Eradication of H. pylori has been shown to reduce the risk of duodenal ulcer recurrence.

H. pylori Eradication Rates – Triple Therapy (amoxicillin/clarithromycin/lansoprazole)

Percent of Patients Cured [95% Confidence Interval] (Number of Patients)

Study | Triple Therapy | Triple Therapy
Evaluable Analysis* | Intent-to-Treat Analysis†
Study 1 | 92‡ [80.0 to 97.7] (n = 48) | 86‡ [73.3 to 93.5] (n = 55)
Study 2 | 86§ [75.7 to 93.6] (n = 66) | 83§ [72.0 to 90.8] (n = 70)
* This analysis was based on evaluable patients with confirmed duodenal ulcer (active or within 1 year) and H. pylori infection at baseline defined as at least 2 of 3 positive endoscopic tests from CLOtest®, (Delta West Ltd., Bentley, Australia), histology, and/or culture. Patients were included in the analysis if they completed the study. Additionally, if patients dropped out of the study due to an adverse event related to the study drug, they were included in the analysis as failures of therapy.
† Patients were included in the analysis if they had documented H. pylori infection at baseline as defined above and had a confirmed duodenal ulcer (active or within 1 year). All dropouts were included as failures of therapy.
‡ (p < 0.05) versus lansoprazole/amoxicillin and lansoprazole/clarithromycin dual therapy.
§ (p < 0.05) versus clarithromycin/amoxicillin dual therapy.

H. pylori Eradication Rates – Dual Therapy (amoxicillin/lansoprazole)

Percent of Patients Cured [95% Confidence Interval] (Number of Patients)

Study | Dual Therapy | Dual Therapy
Evaluable Analysis* | Intent-to-Treat Analysis†
Study 1 | 77‡ [62.5 to 87.2] (n = 51) | 70‡ [56.8 to 81.2] (n = 60)
Study 2 | 66§ [51.9 to 77.5] (n = 58) | 61§ [48.5 to 72.9] (n = 67)
* This analysis was based on evaluable patients with confirmed duodenal ulcer (active or within 1 year) and H. pylori infection at baseline defined as at least 2 of 3 positive endoscopic tests from CLOtest®, histology, and/or culture. Patients were included in the analysis if they completed the study. Additionally, if patients dropped out of the study due to an adverse event related to the study drug, they were included in the analysis as failures of therapy.
† Patients were included in the analysis if they had documented H. pylori infection at baseline as defined above and had a confirmed duodenal ulcer (active or within 1 year). All dropouts were included as failures of therapy.
‡ (p < 0.05) versus lansoprazole alone.
§ (p < 0.05) versus lansoprazole alone or amoxicillin alone.

REFERENCES

1. National Committee for Clinical Laboratory Standards. Methods for Dilution Antimicrobial Susceptibility Tests for Bacteria that Grow Aerobically - Fourth Edition; Approved Standard NCCLS Document M7- A4, Vol. 17, No. 2. NCCLS, Wayne, PA, January 1997.
2. National Committee for Clinical Laboratory Standards. Performance Standards for Antimicrobial Disk Susceptibility Tests - Sixth Edition; Approved Standard NCCLS Document M2-A6, Vol. 17, No. 1. NCCLS, Wayne, PA, January 1997.
3. Swanson-Biearman B, Dean BS, Lopez G, Krenzelok EP. The effects of penicillin and cephalosporin ingestions in children less than six years of age. Vet Hum Toxicol. 1988;30:66-67.

CLINITEST® is a registered trademark of Miles, Inc.
CLINISTIX® is a registered trademark of Bayer Corporation.
CLOtest® is a registered trademark of Kimberly-Clark Corporation.

Consumers and healthcare practitioners may request information or report adverse events, product defects, or problems they suspect are associated with the use of this product by calling 866-848-1909.

Manufactured for:
Bi-Coastal Pharma International LLC
1161 Broad Street
Shrewsbury, NJ 07702

February 2016 L02I R-0909A

Principal Display Panel

NDC: 70934-084-21